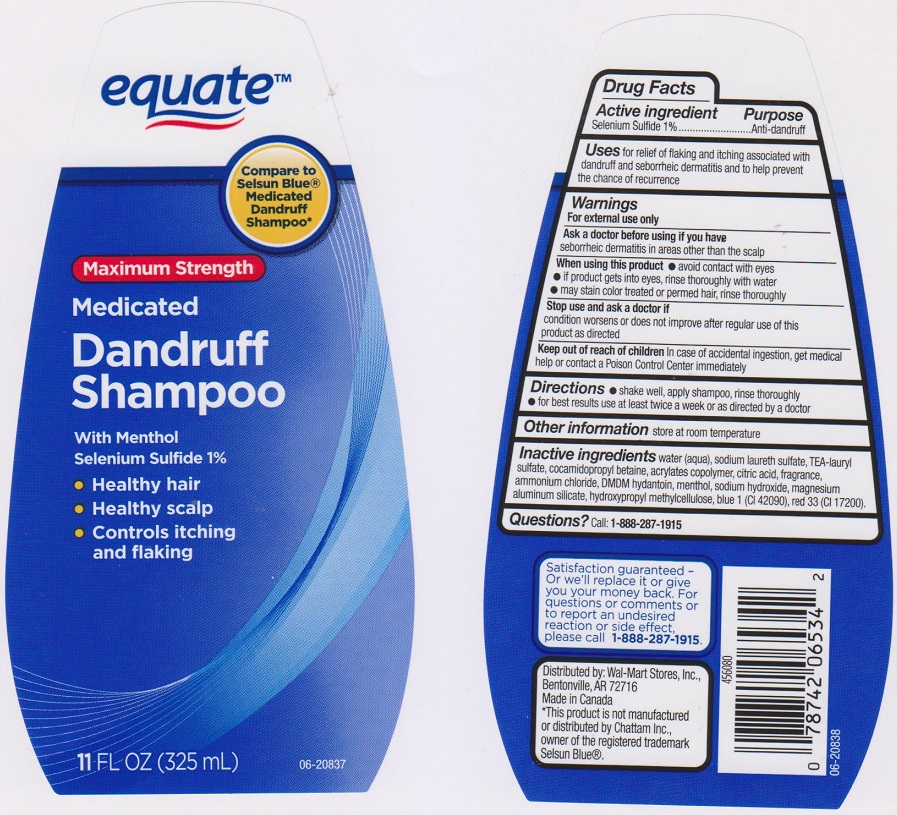 DRUG LABEL: EQUATE
NDC: 49035-719 | Form: LIQUID
Manufacturer: WAL-MART STORES INC
Category: otc | Type: HUMAN OTC DRUG LABEL
Date: 20151112

ACTIVE INGREDIENTS: SELENIUM SULFIDE 10 mg/1 mL
INACTIVE INGREDIENTS: WATER; SODIUM LAURETH SULFATE; TEA-LAURYL SULFATE; COCAMIDOPROPYL BETAINE; METHACRYLIC ACID - METHYL METHACRYLATE COPOLYMER (1:1); CITRIC ACID MONOHYDRATE; AMMONIUM CHLORIDE; DMDM HYDANTOIN; MENTHOL; SODIUM HYDROXIDE; MAGNESIUM ALUMINUM SILICATE; HYPROMELLOSES; FD&C BLUE NO. 1; D&C RED NO. 33

DRUG FACTS

Active ingredient

Selenium Sulfide 1%

Purpose

Anti-dandruff

Uses

for relief of flaking and itching associated with dandruff and seborrheic dermatitis and to help prevent the chance of reccurence

Warnings

For external use only

Ask a doctor before using if you have

seborrheic dermatitis in areas other than the scalp

When using this product

- avoid contact with eyes
- if product gets into eyes, rinse thoroughly with water
- may stain color treated or permed hair, rinse thoroughly

Stop use and ask a doctor if

condition worsens or does not improve after regular use of this product as directed

Keep out of reach of children

In case of accidental ingestion, get medical help or contact a Poison Control Center immediately

Directions

Shake well, apply shampoo, rinse thoroughly. For best results use at least twice a week or as directed by doctor.

Other information

store at room temperature

Inactive ingredients

Water (Aqua), Sodium Laureth Sulfate, TEA-Lauryl Sulfate, Cocamidopropyl Betaine, Acrylates Copolymer, Citric Acid, Fragrance, Ammonium Chloride, DMDM Hydantoin, Menthol, Sodium Hydroxide, Magnesium Aluminum Silicate, Hydroxypropyl Methylcellulose, Blue 1 (CI 42090), Red 33 (CI 17200).

Questions?

Call: 1-888-287-1915